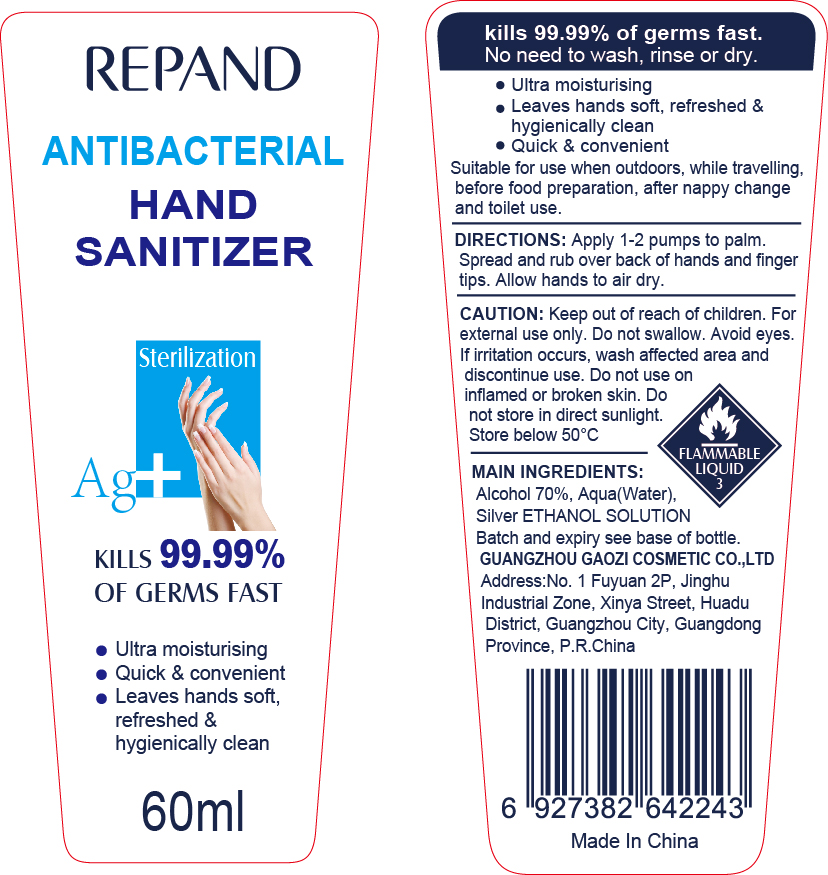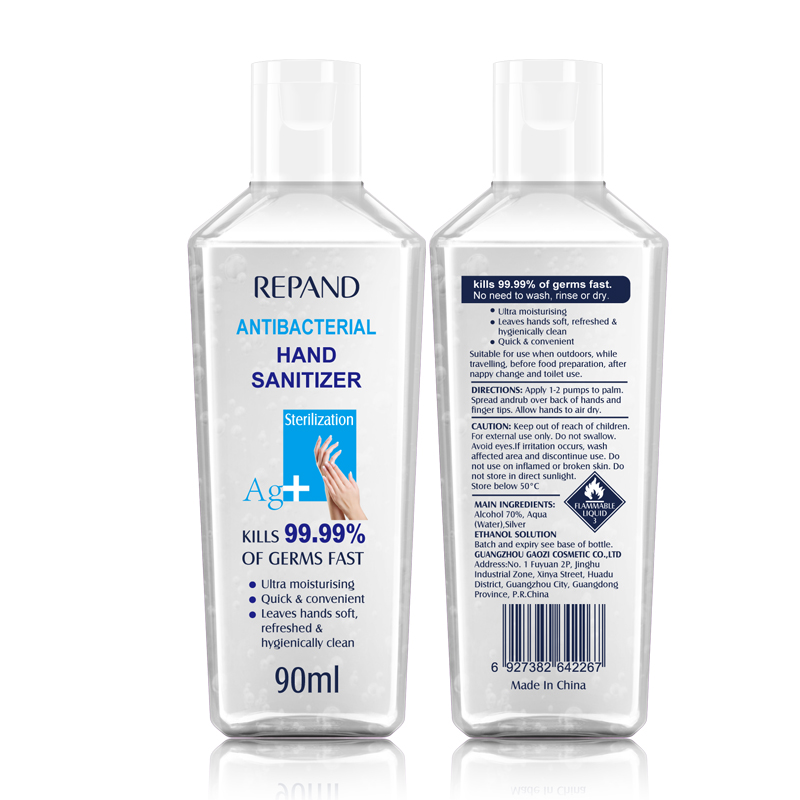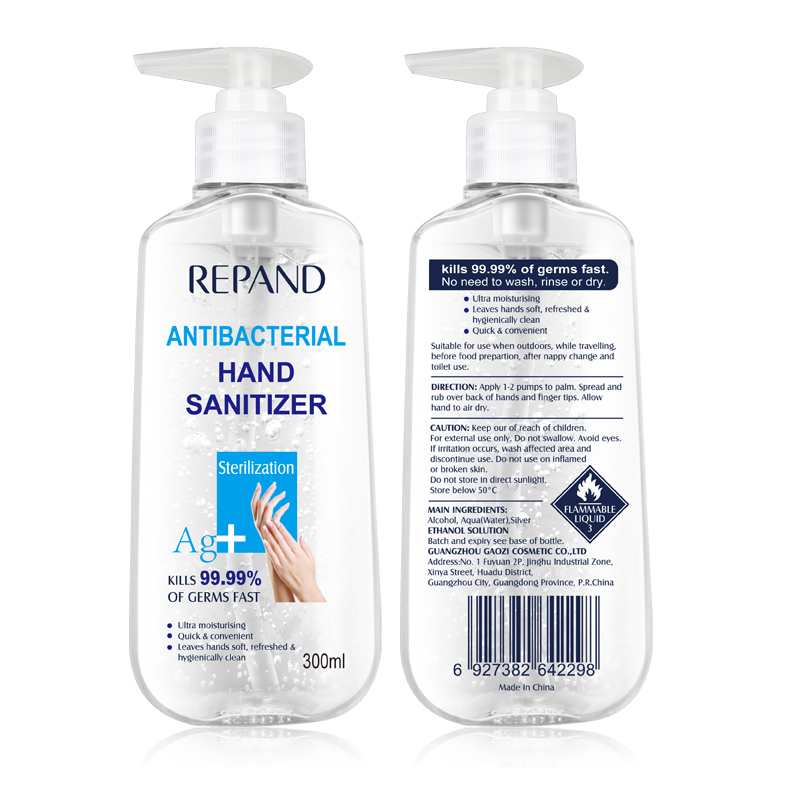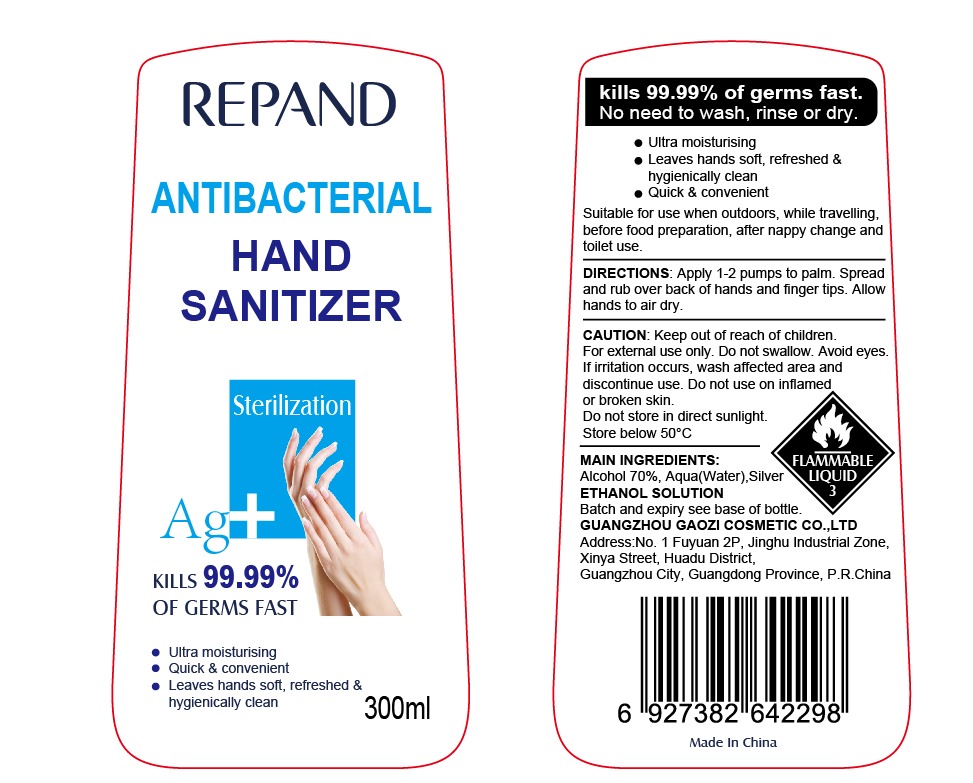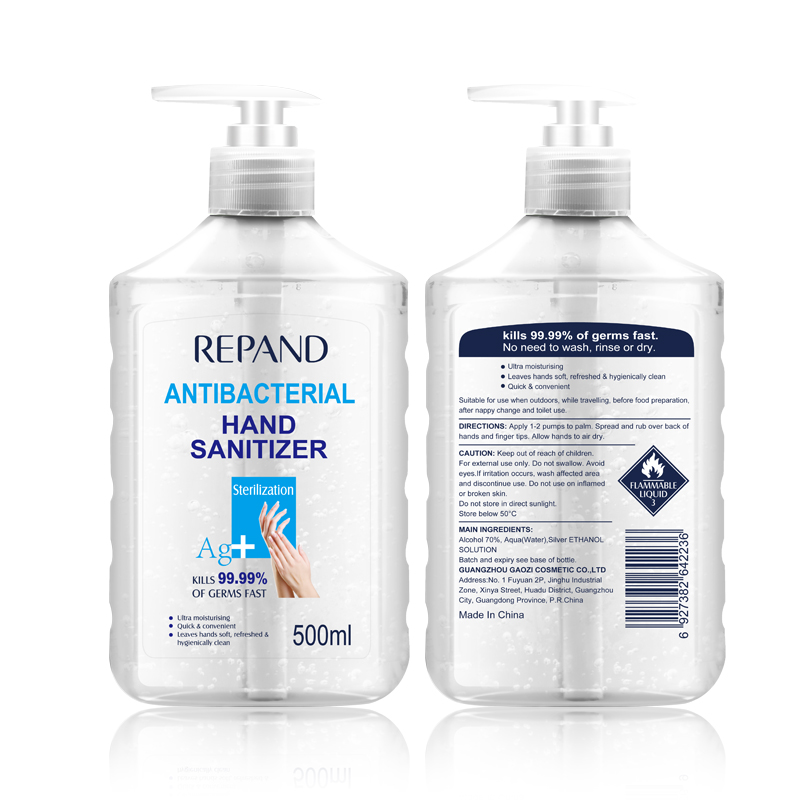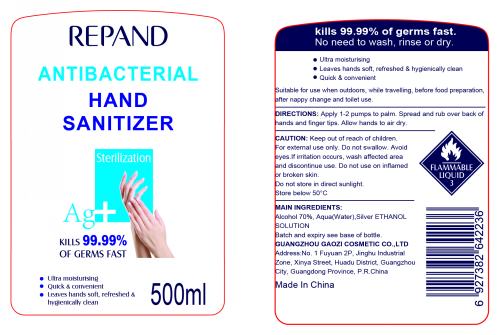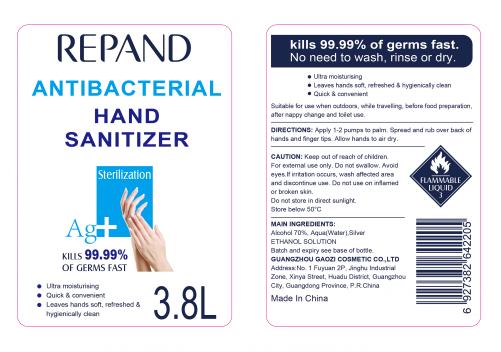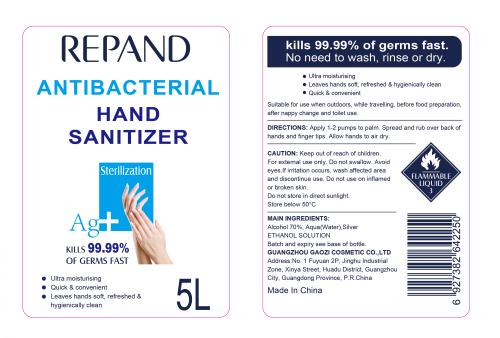 DRUG LABEL: REPAND ANTIBACTERIAL HAND SANITIZER
NDC: 74760-001 | Form: GEL
Manufacturer: GUANGZHOU GAOZI COSMETICS CO., LTD
Category: otc | Type: HUMAN OTC DRUG LABEL
Date: 20200330

ACTIVE INGREDIENTS: ALCOHOL 70 mL/100 mL
INACTIVE INGREDIENTS: WATER

REPAND ANTIBACTERIAL HAND SANITIZER

Active Ingredient

Alcohol 70%

Uses

Suitable for use when outdoors, while travelling,before food preparation, after nappy change and toilet use.

Directions

Apply 1-2 pumps to palm.Spread and rub over back of hands and finger tips.Allow hands to air dry.

Other information

Keep out of reach of children.For external use only.Do not swallow.Avoid eyes. If irritation occurs, wash affected area and

discontinue use.Do not use on inflamed or broken skin.Do not store in direct sunlight. Store below 50°C.

Inactive ingredients

Aqua(Water),Silver ETHANOL SOLUTION Batch and expiry see base of bottle.